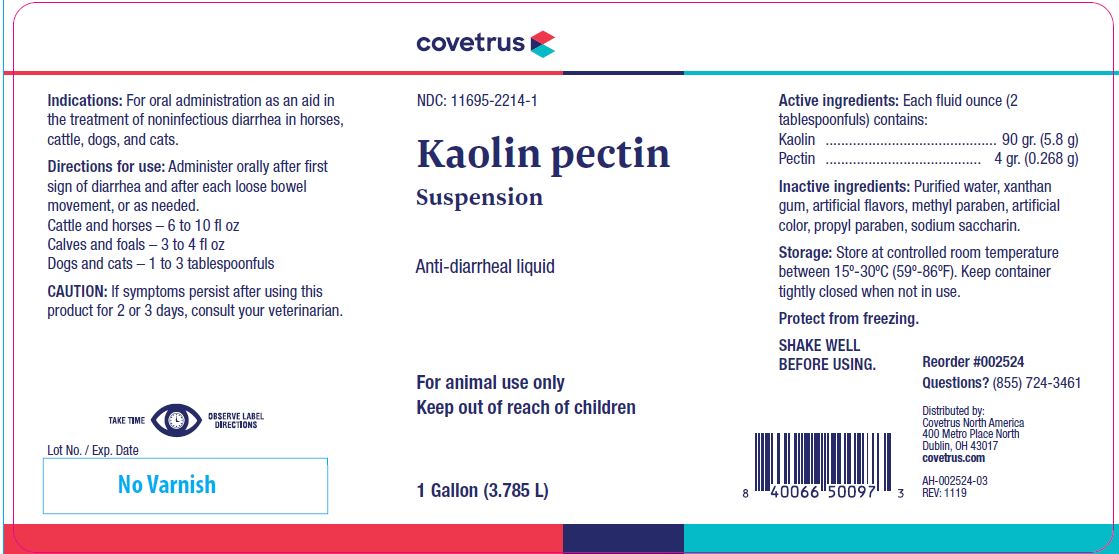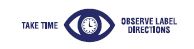 DRUG LABEL: Kaolin pectin
NDC: 11695-2214 | Form: SUSPENSION
Manufacturer: Butler Animal Health Supply, LLC dba Covetrus North America
Category: animal | Type: OTC ANIMAL DRUG LABEL
Date: 20191226

ACTIVE INGREDIENTS: KAOLIN 208.1 g/1 L; PECTIN 8.8 g/1 L

Kaolin pectin
Suspension

STATEMENT OF IDENTITY

Anti-diarrheal liquid

KEEP OUT OF REACH OF CHILDREN

For animal use only
Keep out of reach of children

HOW SUPPLIED

1 Gallon (3.785 L)

Indications:

For oral administration as an aid in the treatment of noninfectious diarrhea in horses, cattle, dogs, and cats.

Directions for use:

Administer orally after first sign of diarrhea and after each loose bowel movement, or as needed.
Cattle and horses – 6 to 10 fl oz
Calves and foals – 3 to 4 fl oz
Dogs and cats – 1 to 3 tablespoonfuls

CAUTION:

If symptoms persist after using this product for 2 or 3 days, consult your veterinarian.

Active ingredients:

Each fluid ounce (2 tablespoonfuls) contains:
Kaolin ............................................ 90 gr. (5.8 g)
Pectin ........................................ 4 gr. (0.268 g)

Inactive ingredients:

Purified water, xanthan gum, artificial flavors, methyl paraben, artificial color, propyl paraben, sodium saccharin.

Storage:

Store at controlled room temperature between 15º-30ºC (59º-86ºF). Keep container tightly closed when not in use.

Protect from freezing.
SHAKE WELL BEFORE USING.

INFORMATION FOR OWNERS/CAREGIVERS

Reorder #002524
Questions? (855) 724-3461
Distributed by:
Covetrus North America
400 Metro Place North
Dublin, OH 43017
covetrus.com

AH-002524-03
REV: 1119